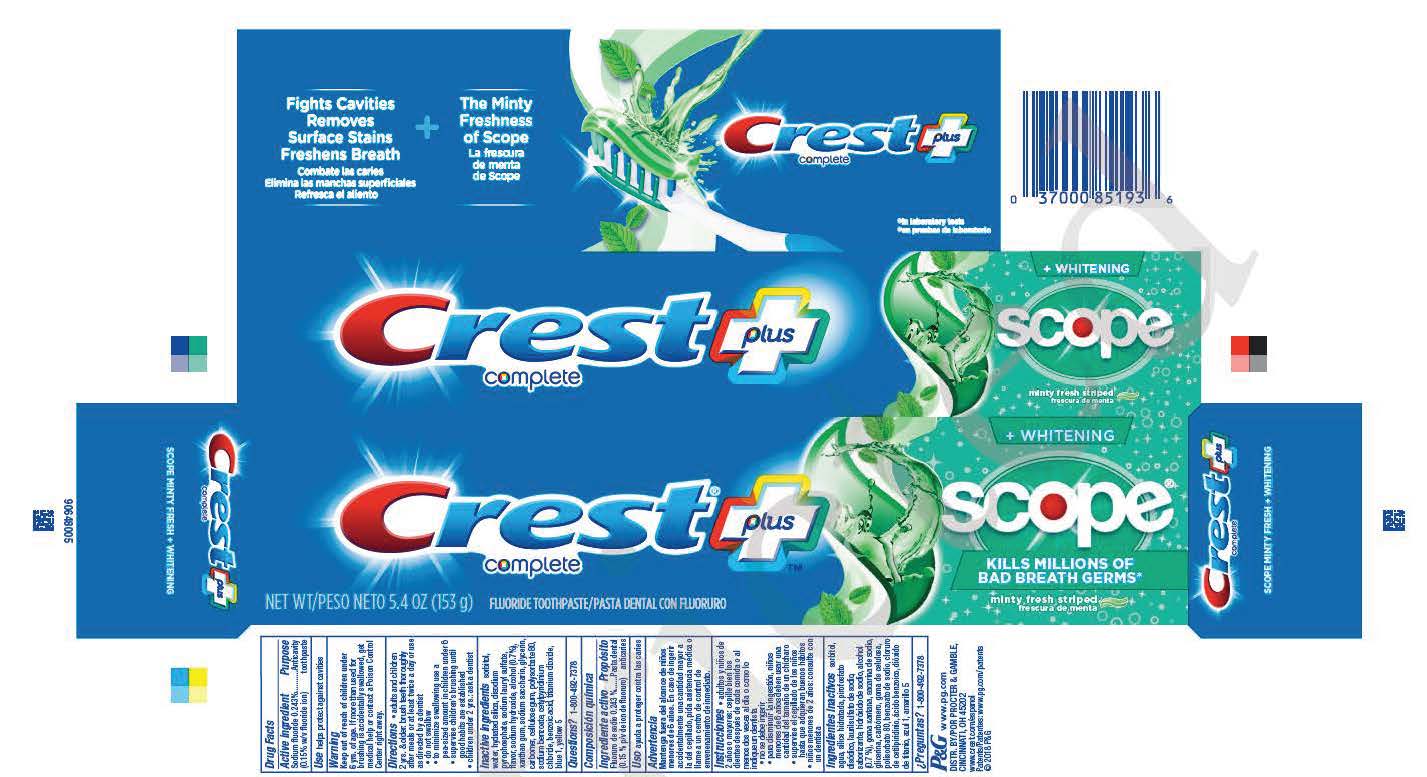 DRUG LABEL: Crest Complete Multi-Benefit
NDC: 58933-020 | Form: PASTE, DENTIFRICE
Manufacturer: Procter & Gamble Manufactura, S. de R.L. de C.V.
Category: otc | Type: HUMAN OTC DRUG LABEL
Date: 20260205

ACTIVE INGREDIENTS: SODIUM FLUORIDE 1.5 mg/1 g
INACTIVE INGREDIENTS: SORBITOL; WATER; HYDRATED SILICA; SODIUM ACID PYROPHOSPHATE; SODIUM LAURYL SULFATE; SODIUM HYDROXIDE; ALCOHOL; XANTHAN GUM; SACCHARIN SODIUM; GLYCERIN; CARBOXYMETHYLCELLULOSE SODIUM; POLYSORBATE 80; SODIUM BENZOATE; CETYLPYRIDINIUM CHLORIDE; BENZOIC ACID; TITANIUM DIOXIDE; FD&C BLUE NO. 1; FD&C YELLOW NO. 5

Crest® Complete plus
Whitening plus Scope®

Active ingredient

Sodium fluoride 0.243%
(0.15% w/v fluoride ion)

Purpose

Anticavity toothpaste

Warning

Keep out of reach of children under 6 yrs. of age. If more than used for brushing is accidentally swallowed, get medical help or contact a Poison Control Center right away.

Directions

- adults and children 2 yrs. & older: brush teeth thoroughly after meals or at least twice a day or use as directed by a dentist
- do not swallow
- to minimize swallowing use a pea-sized amount in children under 6
- supervise children’s brushing until good habits are established
- children under 2 yrs.: ask a dentist

Inactive ingredients

sorbitol, water, hydrated silica, disodium pyrophosphate, sodium lauryl sulfate, flavor, sodium hydroxide, alcohol (0.7%), xanthan gum, sodium saccharin, glycerin, carbomer, cellulose gum, polysorbate 80, sodium benzoate, cetylpyridinium chloride, benzoic acid, titanium dioxide, blue 1, yellow 5

Questions?

1-800-492-7378

DISTR. BY/POR PROCTER & GAMBLE,
CINCINNATI, OH 45202

PRINCIPAL DISPLAY PANEL - 153 g Tube Carton

Crest complete plus

+ WHITENING

SCOPE

NET WT/PESO NETO 5.4 OZ (153 g)

FLUORIDE TOOTHPASTE/PASTA DENTAL CON FLUORURO

KILLS MILLIONS OF

BAD BREATH GERMS*

minty fresh striped

frescura de menta